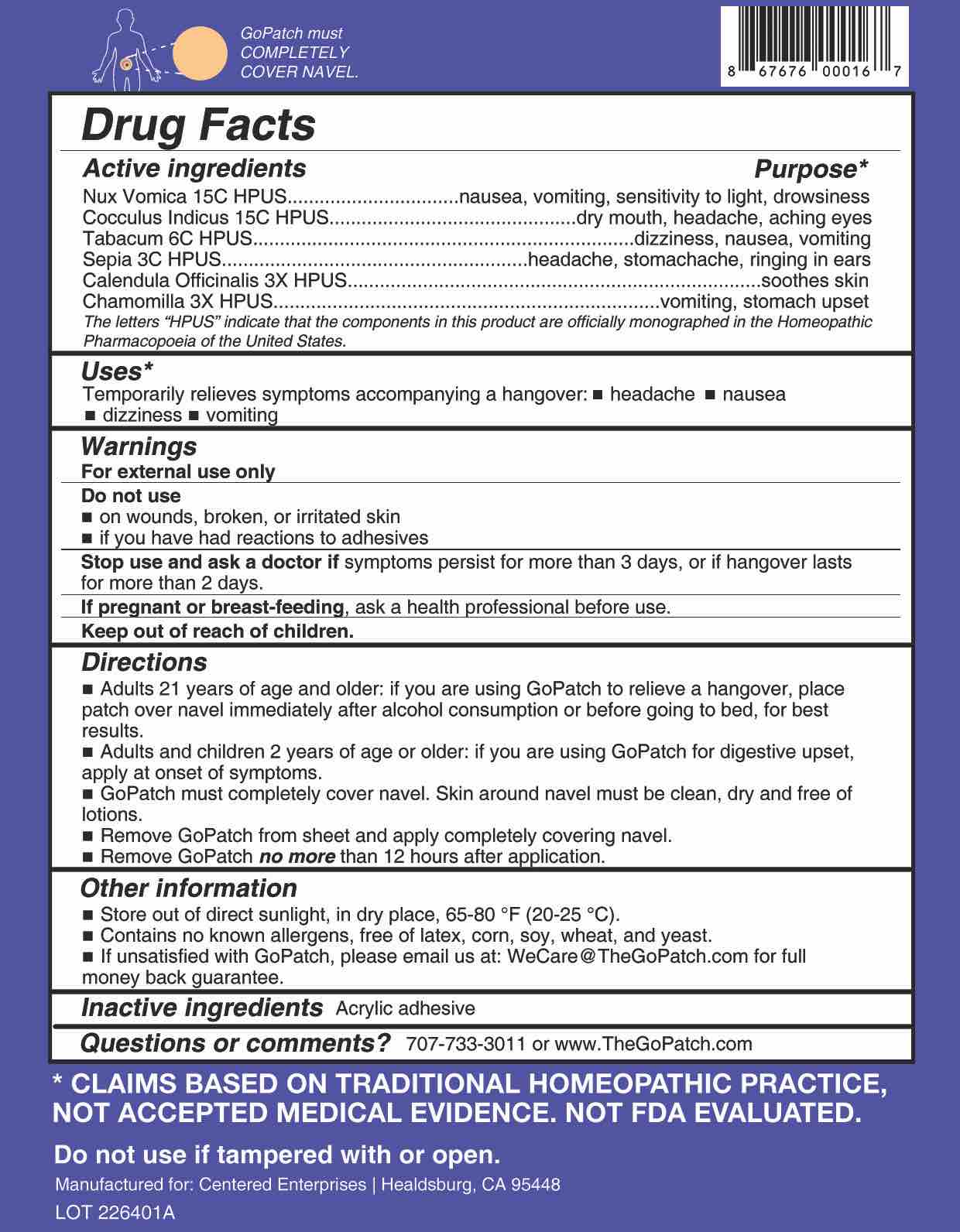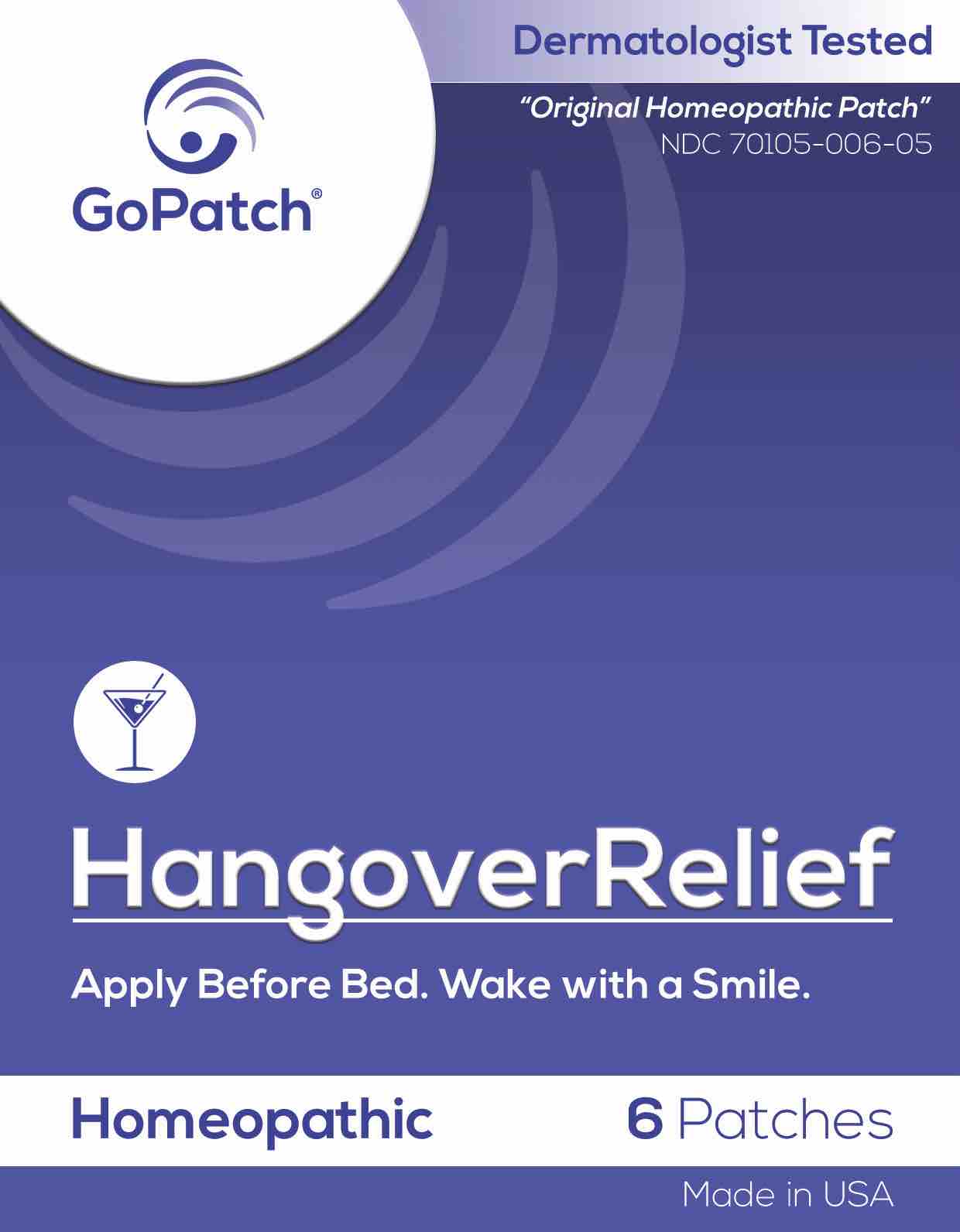 DRUG LABEL: GoPatch HangoverRelief
NDC: 70105-006 | Form: PATCH
Manufacturer: Centered Enterprises, LLC
Category: homeopathic | Type: HUMAN OTC DRUG LABEL
Date: 20240115

ACTIVE INGREDIENTS: CALENDULA OFFICINALIS FLOWERING TOP 3 [hp_X]/1 1; MATRICARIA RECUTITA 3 [hp_X]/1 1; SEPIA OFFICINALIS JUICE 3 [hp_C]/1 1; TOBACCO LEAF 6 [hp_C]/1 1; ANAMIRTA COCCULUS SEED 15 [hp_C]/1 1; STRYCHNOS NUX-VOMICA SEED 15 [hp_C]/1 1
INACTIVE INGREDIENTS: POLYVINYL ACETATE; WATER; ALCOHOL

Hangover Relief

Active ingredients | Purpose*
Nux Vomica 15C HPUS | nausea, vomiting, sensitivity to light, drowsiness
Cocculus Indicus 15C HPUS | dry mouth, headache, aching eyes
Tabacum 6C HPUS | dizziness, nausea, vomiting
Sepia 3C HPUS | headache, stomachache, ringing in ears
Calendula Officinalis 3X HPUS | soothes skin
Chamomilla 3X HPUS | vomitting, stomach upset

The letters "HPUS" indicate that the components in this product are officially monographed in the Homeopathic Pharmacopoeia of the United States.

Purpose

Nux Vomica - nausea, vomiting, sensitivity to light, drowsiness

Cocculus Indicus - dry mouth, headache, aching eyes

Tabacum - dizziness, nausea, vomiting

Sepia - headache, stomachache, ringing in ears

Calendula Officinalis - soothes skin

Chamomilla - vomitting, stomach upset

Uses

Temporarily relieves symptoms accompanying a hangover: ■ headache ■ nausea ■ dizziness ■ vomiting

Warnings

- For external use only.

Do Not Use

■ on wounds, broken, or irritated skin
■ if you have had reactions to adhesives

Stop Use

Stop use and ask a doctor if symptoms persist for more than 3 days, or hangover lasts more than 2 days..

If pregnant or breast-feeding, ask a health professional before use.

- Keep out of reach of children.

Directions

■ Adults 21 years of age or older: if you are using GoPatch to relieve a hangover, place patch over navel immediately after alcohol consumption or before going to bed, for best results.
■ Adults and children 2 years of age and older: If you are using GoPatch for digestive upset, apply at onset of symptoms.

■ GoPatch must completely cover navel. Skin around navel must be clean, dry, and free of lotions.
■ Remove GoPatch from sheet and apply completely covering navel.
■ Remove GoPatch no more than 12 hours after application.

Other information

- Store out of direct sunlight, in dry place, at 65-80°F (20-25°C).
- Contains no known allergens, free of latex, corn, soy, wheat, and yeast.
- If unsatisfied with GoPatch, please email us at WeCare@TheGoPatch.com for full money back guarantee.

Questions?

Questions or comments? Please call us at (707) 733-3011 or www.TheGoPatch.com

Inactive ingredients Acrylic adhesive

PACKAGE LABEL

GoPatch™

NDC 70105-006-05

Homeopathic